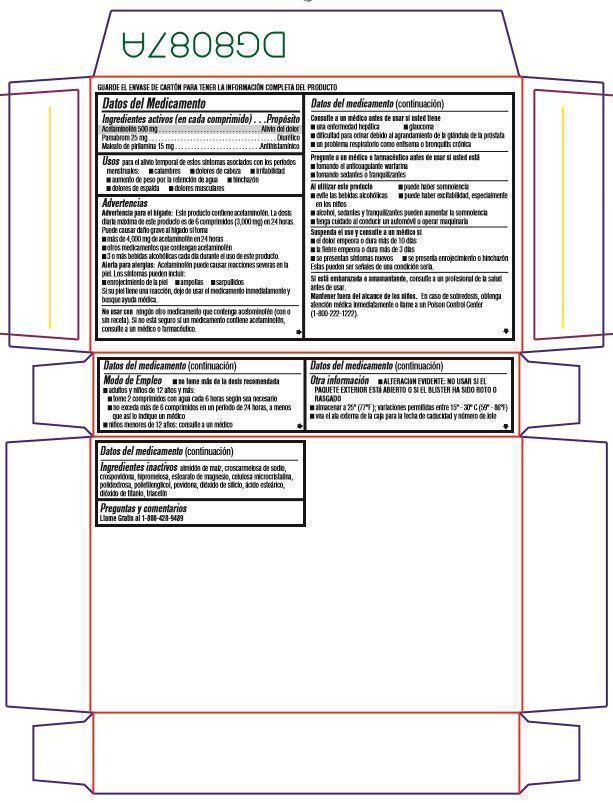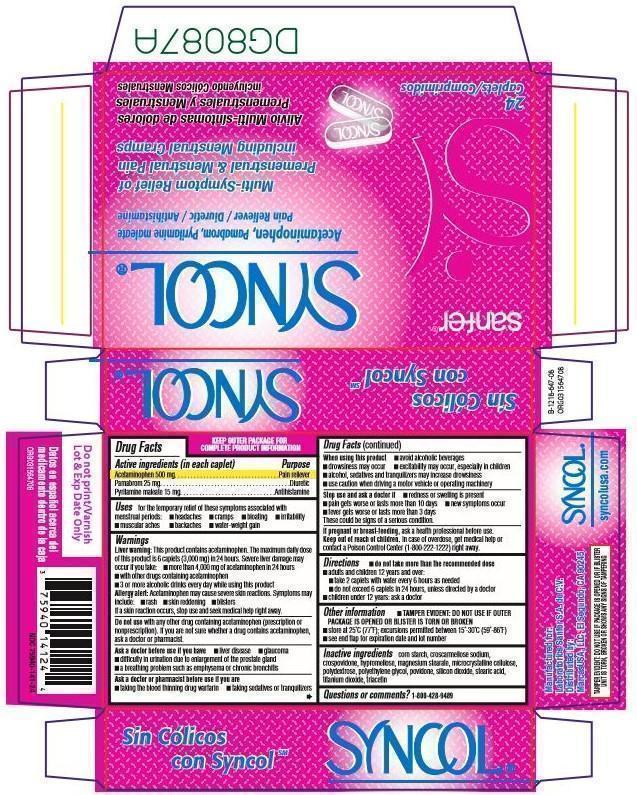 DRUG LABEL: Syncol
NDC: 75940-141 | Form: CAPSULE
Manufacturer: MarcasUSA LLC
Category: otc | Type: HUMAN OTC DRUG LABEL
Date: 20150709

ACTIVE INGREDIENTS: ACETAMINOPHEN 500 mg/1 1; PAMABROM 25  mg/1 1; PYRILAMINE MALEATE 15  mg/1 1
INACTIVE INGREDIENTS: STARCH, CORN; CROSCARMELLOSE SODIUM; CROSPOVIDONE; HYPROMELLOSES; MAGNESIUM STEARATE; CELLULOSE, MICROCRYSTALLINE; POLYDEXTROSE; POLYETHYLENE GLYCOLS; POVIDONE; SILICON DIOXIDE; STEARIC ACID; TITANIUM DIOXIDE; TRIACETIN

SYNCOL

Drug Facts

Active ingredients (in each caplet) | Purpose

PURPOSE

Acetaminophen 500 mg ..........................................Pain reliever

Pamabrom 25 mg ....................................................Diuretic

Pyrilamine maleate15 mg........................................Antihistamine

Uses

for the temporary relief of these symptoms associated with menstrual periods:

- cramps
- headache
- bloating
- backache
- water-weight gain
- muscular aches
- irritability

Warnings

Liver warning: This product contains acetaminophen. The maximum daily dose
of this product is 6 caplets (3,000 mg) in 24 hours. Severe liver damage may
occur if you take:

- more than 4,000 mg of acetaminophen in 24 hours
- with other drugs containing acetaminophen
- 3 or more alcoholic drinks every day while using this product

Allergy alert: Acetaminophen may cause severe skin reactions. Symptoms may
include:

- rash
- skin reddening
- blisters

If a skin reaction occurs, stop use and seek medical help right away.

Do not use

with any other drug containing acetaminophen (prescription or nonprescription). If you are not sure whether a drug contains acetaminophen, ask a doctor or pharmacist.

Ask a doctor before use if you have

- liver disease
- glaucoma
- difficulty in urination due to enlargement of the prostate gland
- a breathing problem such as emphysema or chronic bronchitis

Ask a doctor or pharmacist before use if you are

- taking the blood thinning drug warfarin
- taking sedatives or tranquilizers

When using this product

- avoid alcoholic beverages
- drowsiness may occur
- excitability may occur, especially in children
- alcohol, sedatives and tranquilizers may increase drowsiness
- use caution when driving or operating machinery

Stop use and ask a doctor if

- redness or swelling is present
- pain gets worse or lasts more than 10 days
- fever gets worse or lasts more than 3 days
- new symptoms occur

These could be signs of a serious condition.

If pregnant or breast-feeding,

ask a health professional before use.

Keep out of reach of children.

In case of overdose, get medical help or
contact a Poison Control Center (1-800-222-1222) right away.

Directions

- do not take more than the recommended dose

- adults and children 12 years and over:
- take 2 caplets with water every 6 hours as needed
- do not exceed 6 caplets in 24 hours, unless directed by a doctor

- children under 12 years: ask a doctor

Other information

- TAMPER EVIDENT: DO NOT USE IF OUTER PACKAGE IS OPENED OR BLISTER IS TORN OR BROKEN
- store at 25°C (77°F); excursions permitted between 15°-30°C (59°-86°F)
- see end flap for expiration date and lot number

Inactive ingredients

corn starch, croscarmellose sodium,
crospovidone, hypromellose, magnesium stearate, microcrystalline cellulose,
polydextrose, polyethylene glycol, povidone, silicon dioxide, stearic acid,
titanium dioxide, triacetin

Questions or comments?

1-800-428-9489

Datos del Medicamento

Ingredientes activos (en cada comprimido) | Propósito

Acetaminofén 500 mg . . . . . . . . . . . . . . . . . . . . . . . . . . . . . . . . Alivio del dolor
Pamabrom 25 mg . . . . . . . . . . . . . . . . . . . . . . . . . . . . . . . . . . . . . . . . Diurético
Maleato de pirilamina 15 mg . . . . . . . . . . . . . . . . . . . . . . . . . . .Antihistamínico

Usos

para el alivio temporal de estos síntomas asociados con los períodos
menstruales:

- calambres
- dolores de cabeza
- irritabilidad
- aumento de peso por la retención de agua
- hinchazón
- dolores de espalda
- dolores musculares

Advertencias

Advertencia para el hígado: Este producto contiene acetaminofén. La dosis
diaria máxima de este producto es de 6 comprimidos (3,000 mg) en 24 horas.
Puede causar daño grave al hígado si toma

- más de 4,000 mg de acetaminofén en 24 horas
- otros medicamentos que contengan acetaminofén
- 3 o más bebidas alcohólicas cada día durante el uso de este producto.

Alerta para alergias: Acetaminofén puede causar reacciones severas en la
piel. Los síntomas pueden incluir:

- enrojecimiento de la piel
- ampollas
- sarpullidos

Si su piel tiene una reacción, deje de usar el medicamento inmediatamente y
busque ayuda médica.

No usar con ningún otro medicamento que contenga acetominofén (con o
sin receta). Si no está seguro si un medicamento contiene acetaminofén,
consulte a un médico o farmacéutico.

Consulte a un médico antes de usar si usted tiene

- una enfermedad hepática
- glaucoma
- dificultad para orinar debido al agrandamiento de la glándula de la próstata
- un problema respiratorio como enfisema o bronquitis crónica

Pregunte a un médico o farmacéutico antes de usar si usted está

- tomando el anticoagulante warfarina
- tomando sedantes o tranquilizantes

Al utilizar este producto

- puede haber somnolencia
- evite las bebidas alcohólicas
- puede haber excitabilidad, especialmente en los niños
- alcohol, sedantes y tranquilizantes pueden aumentar la somnolencia
- tenga cuidado al conducir un automóvil u operar maquinaria

Suspenda el uso y consulte a un médico si

- el dolor empeora o dura más de 10 días
- la fiebre empeora o dura más de 3 días
- se presentan síntomas nuevos
- se presenta enrojecimiento o hinchazón

Estas pueden ser señales de una condición seria.

Si está embarazada o amamantando, consulte a un profesional de la salud
antes de usar.
Mantener fuera del alcance de los niños. En caso de sobredosis, obtenga
atención médica inmediatamente o llame a un Poison Control Center
(1-800-222-1222).

Modo de Empleo

- no tome más de la dosis recomendada
- adultos y niños de 12 años y más:
  - tome 2 comprimidos con agua cada 6 horas según sea necesario
  - no exceda más de 6 comprimidos en un período de 24 horas, a menos
    que así lo indique un medico
- niños menores de 12 años: consulte a un médico

Otra información

- ALTERACIóN EVIDENTE: NO USAR SI EL
  PAQUETE EXTERIOR ESTá ABIERTO O SI EL BLíSTER HA SIDO ROTO O
  RASGADO
- almacenar a 25° (77°F); variaciones permitidas entre 15° - 30° C (59° - 86°F)
- vea el ala externa de la caja para la fecha de caducidad y número de lote

Ingredientes inactivos almidón de maíz, croscarmelosa de sodio,
crospovidona, hipromelosa, estearato de magnesio, celulosa microcristalina,
polidextrosa, polietilenglicol, povidona, dióxido de silicio, ácido esteárico,
dióxido de titanio, triacetín

Preguntas y comentarios

Llame Gratis al 1-800-428-9489

PACKAGE LABEL PRINCIPAL DISPLAY PANEL - 24 Capsules

SYNCOL ®

Acetaminophen / Pamabrom / Pyrilamine Maleate
Pain Reliever / Diuretic / Antihistamine

Multi-Symptom Relief of
Premenstrual & Menstrual Pain
including Menstrual Cramps

Alivio Multi-síntomas de dolores
Premenstruales y Menstruales
incluyendo Cólicos Menstruales

24 Caplets / Comprimidos